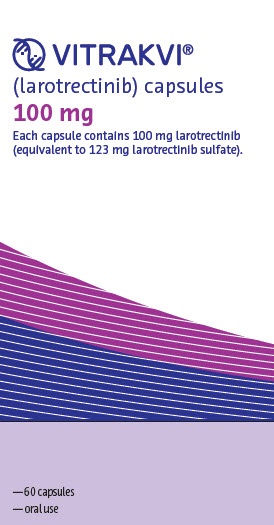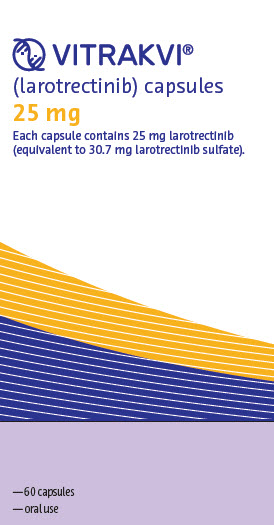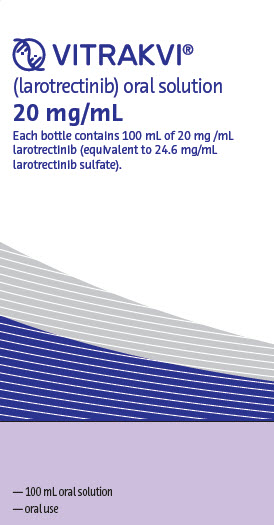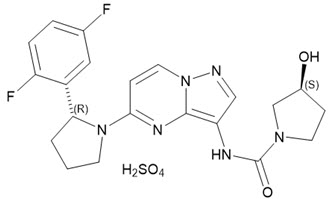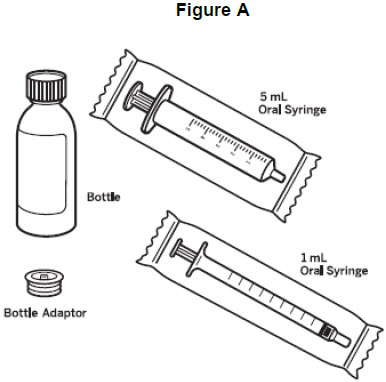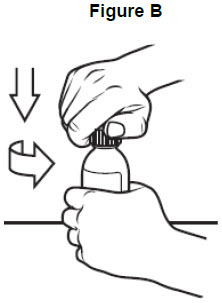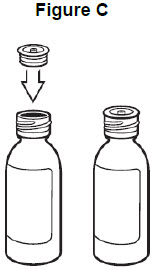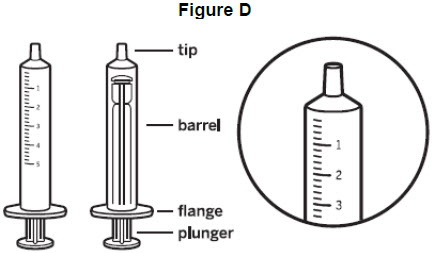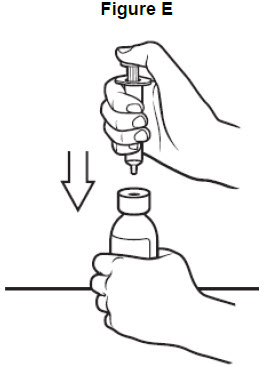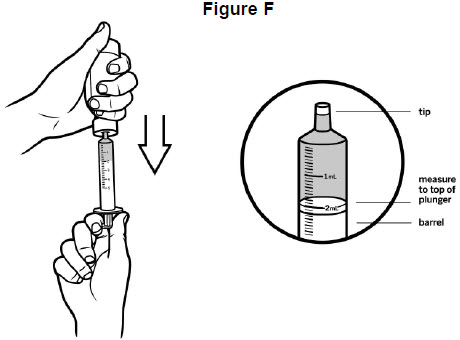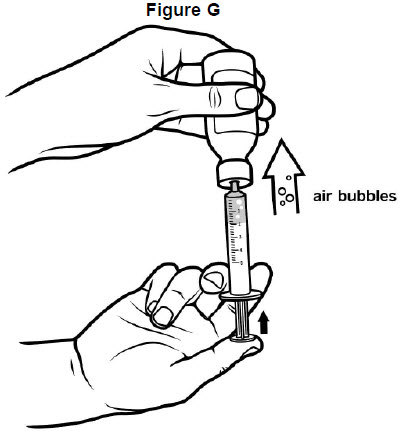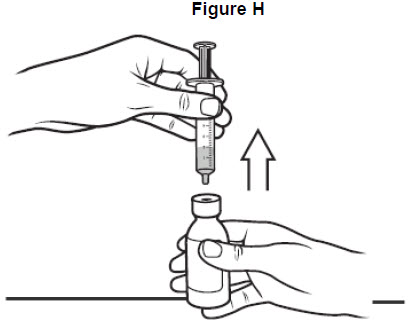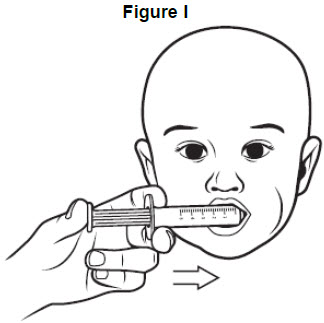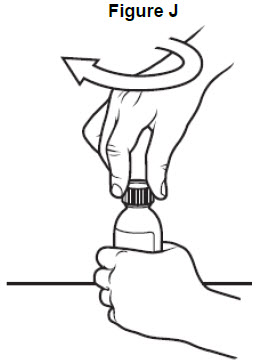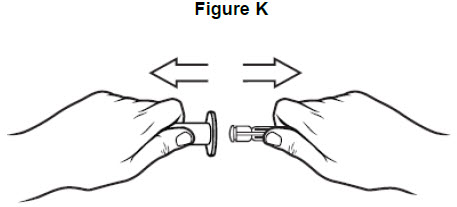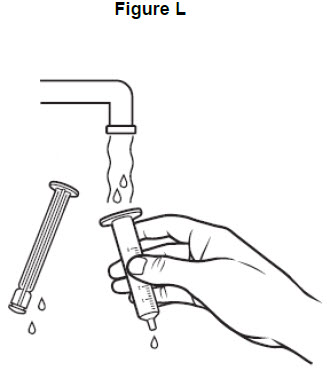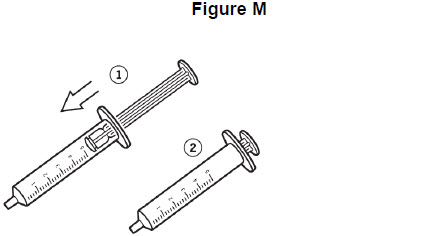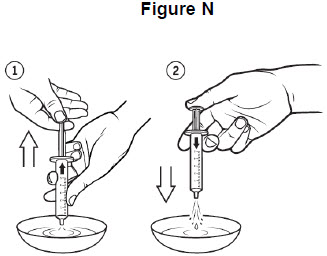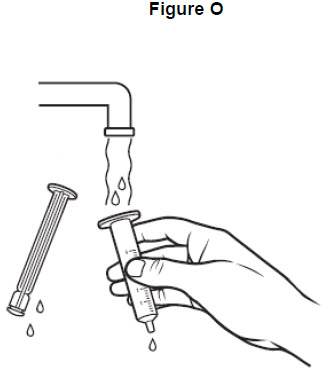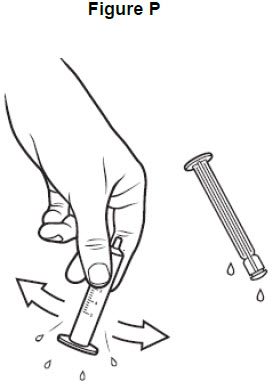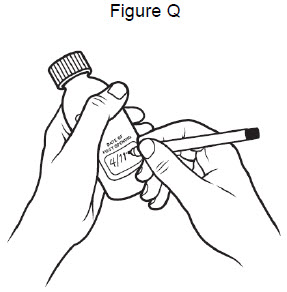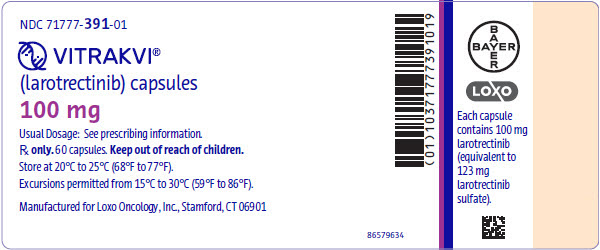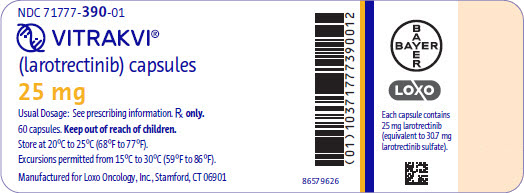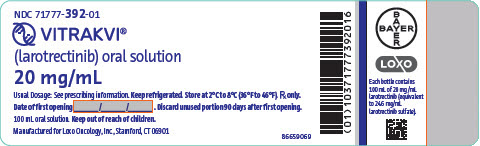 DRUG LABEL: VITRAKVI
NDC: 71777-390 | Form: CAPSULE
Manufacturer: Loxo Oncology, Inc.
Category: prescription | Type: HUMAN PRESCRIPTION DRUG LABEL
Date: 20181205

ACTIVE INGREDIENTS: LAROTRECTINIB 25 mg/1 1
INACTIVE INGREDIENTS: GELATIN, UNSPECIFIED; TITANIUM DIOXIDE

HIGHLIGHTS OF PRESCRIBING INFORMATION

These highlights do not include all the information needed to use VITRAKVI safely and effectively. See full prescribing information for VITRAKVI.
VITRAKVI® (larotrectinib) capsules, for oral use
VITRAKVI® (larotrectinib) oral solution
Initial U.S. Approval: 2018

1 INDICATIONS AND USAGE

VITRAKVI is a kinase inhibitor indicated for the treatment of adult and pediatric patients with solid tumors that:

- have a neurotrophic receptor tyrosine kinase (NTRK) gene fusion without a known acquired resistance mutation,
- are metastatic or where surgical resection is likely to result in severe morbidity, and
- have no satisfactory alternative treatments or that have progressed following treatment.

This indication is approved under accelerated approval based on overall response rate and duration of response. Continued approval for this indication may be contingent upon verification and description of clinical benefit in confirmatory trials (1,14).

2 DOSAGE AND ADMINISTRATION

- Select patients for treatment with VITRAKVI based on the presence of a NTRK gene fusion (2.1, 14).
- Recommended Dosage in Adult and Pediatric Patients with Body Surface Area of at Least 1.0 Meter-Squared: 100 mg orally twice daily (2.2)
- Recommended Dosage in Pediatric Patients with Body Surface Area of Less Than 1.0 Meter-Squared: 100 mg/m^2 orally twice daily (2.2)

3 DOSAGE FORMS AND STRENGTHS

- Capsules: 25 mg, 100 mg (3)
- Oral Solution: 20 mg/mL (3)

4 CONTRAINDICATIONS

None. (4)

5 WARNINGS AND PRECAUTIONS

- Neurotoxicity: Advise patients and caretakers of the risk of neurologic adverse reactions. Advise patients not to drive or operate hazardous machinery if experiencing neurotoxicity. Withhold and modify dosage, or permanently discontinue VITRAKVI based on severity. (2.3, 5.1)
- Hepatotoxicity: Monitor liver tests including ALT and AST every 2 weeks during the first month of treatment, then monthly thereafter and as clinically indicated. Withhold and modify dosage, or permanently discontinue VITRAKVI based on severity. (2.6, 5.2)
- Embryo-Fetal Toxicity: Can cause fetal harm. Advise females with reproductive potential of potential risk to the fetus and to use effective contraception. (5.3, 8.3)

6 ADVERSE REACTIONS

The most common adverse reactions (≥ 20%) with VITRAKVI were fatigue, nausea, dizziness, vomiting, increased AST, cough, increased ALT, constipation, and diarrhea. (6).

To report SUSPECTED ADVERSE REACTIONS, contact Bayer HealthCare Pharmaceuticals Inc. at 1-888-842-2937 or FDA at 1-800-FDA-1088 or www.fda.gov/medwatch.

7 DRUG INTERACTIONS

- Strong CYP3A4 Inhibitors: Avoid coadministration of strong CYP3A4 inhibitors with VITRAKVI. If coadministration cannot be avoided, reduce the VITRAKVI dose. (2.4, 7.1)
- Strong CYP3A4 Inducers: Avoid coadministration of strong CYP3A4 inducers with VITRAKVI. If coadministration cannot be avoided, increase the VITRAKVI dose. (2.5, 7.1)
- Sensitive CYP3A4 Substrates: Avoid coadministration of sensitive CYP3A4 substrates with VITRAKVI. (7.2)

8 USE IN SPECIFIC POPULATIONS

- Lactation: Advise not to breastfeed. (8.2)
- Hepatic Impairment: Reduce the starting dose of VITRAKVI in patients with moderate (Child-Pugh B) to severe (Child-Pugh C) hepatic impairment. (2.6, 8.7)

FULL PRESCRIBING INFORMATION

1 INDICATIONS AND USAGE

VITRAKVI is indicated for the treatment of adult and pediatric patients with solid tumors that:

- have a neurotrophic receptor tyrosine kinase (NTRK) gene fusion without a known acquired resistance mutation,
- are metastatic or where surgical resection is likely to result in severe morbidity, and
- have no satisfactory alternative treatments or that have progressed following treatment.

This indication is approved under accelerated approval based on overall response rate and duration of response [see Clinical Studies (14)]. Continued approval for this indication may be contingent upon verification and description of clinical benefit in confirmatory trials.

2 DOSAGE AND ADMINISTRATION

2.1 Patient Selection

Select patients for treatment with VITRAKVI based on the presence of a NTRK gene fusion in tumor specimens [see Clinical Studies (14)]. An FDA-approved test for the detection of NTRK gene fusion is not currently available.

2.2 Recommended Dosage

Recommended Dosage in Adult and Pediatric Patients with Body Surface Area of at Least 1.0 Meter-Squared

The recommended dosage of VITRAKVI is 100 mg orally twice daily, with or without food, until disease progression or until unacceptable toxicity.

Recommended Dosage in Pediatric Patients with Body Surface Area Less Than 1.0 Meter-Squared

The recommended dosage of VITRAKVI is 100 mg/m^2 orally twice daily, with or without food, until disease progression or until unacceptable toxicity.

2.3 Dosage Modifications for Adverse Reactions

For Grade 3 or 4 adverse reactions:

- Withhold VITRAKVI until adverse reaction resolves or improves to baseline or Grade 1. Resume at the next dosage modification if resolution occurs within 4 weeks.
- Permanently discontinue VITRAKVI if an adverse reaction does not resolve within 4 weeks.

The recommended dosage modifications for VITRAKVI for adverse reactions are provided in Table 1.

Table 1 Recommended Dosage Modifications for VITRAKVI for Adverse Reactions

Dosage Modification | Adult and Pediatric Patients with Body Surface Area of at Least 1.0 m^2 | Pediatric Patients with Body Surface Area Less Than 1.0 m^2
First | 75 mg orally twice daily | 75 mg/m^2 orally twice daily
Second | 50 mg orally twice daily | 50 mg/m^2 orally twice daily
Third | 100 mg orally once daily | 25 mg/m^2 orally twice daily

Permanently discontinue VITRAKVI in patients who are unable to tolerate VITRAKVI after three dose modifications.

2.4 Dosage Modifications for Coadministration with Strong CYP3A4 Inhibitors

Avoid coadministration of strong CYP3A4 inhibitors with VITRAKVI. If coadministration of a strong CYP3A4 inhibitor cannot be avoided, reduce the VITRAKVI dose by 50%. After the inhibitor has been discontinued for 3 to 5 elimination half-lives, resume the VITRAKVI dose taken prior to initiating the CYP3A4 inhibitor [see Drug Interactions (7.1), Clinical Pharmacology (12.3)].

2.5 Dosage Modifications for Coadministration with Strong CYP3A4 Inducers

Avoid coadministration of strong CYP3A4 inducers with VITRAKVI. If coadministration of a strong CYP3A4 inducer cannot be avoided, double the VITRAKVI dose. After the inducer has been discontinued for 3 to 5 elimination half-lives, resume the VITRAKVI dose taken prior to initiating the CYP3A4 inducer [see Drug Interactions (7.1), Clinical Pharmacology (12.3)].

2.6 Dosage Modifications for Patients with Hepatic Impairment

Reduce the starting dose of VITRAKVI by 50% in patients with moderate (Child-Pugh B) to severe (Child-Pugh C) hepatic impairment [see Use in Specific Populations (8.6), Clinical Pharmacology (12.3)].

2.7 Administration

VITRAKVI capsule or oral solution may be used interchangeably.

Do not make up a missed dose within 6 hours of the next scheduled dose.

If vomiting occurs after taking a dose of VITRAKVI, take the next dose at the scheduled time.

Capsules

Swallow capsules whole with water. Do not chew or crush the capsules.

Oral Solution

- Store the glass bottle of VITRAKVI oral solution in the refrigerator. Discard any unused VITRAKVI oral solution remaining after 90 days of first opening the bottle.
- Prior to preparing an oral dose for administration, refer to the Instructions for Use.

3 DOSAGE FORMS AND STRENGTHS

Capsules

- 25 mg: white opaque hard gelatin capsule, size 2, with blue printing of "LOXO" and "LARO 25 mg" on body of capsules. 25 mg larotrectinib is equivalent to 30.7 mg larotrectinib sulfate.
- 100 mg: white opaque hard gelatin capsule, size 0, with blue printing of "LOXO" and "LARO 100 mg" on body of capsule. 100 mg larotrectinib is equivalent to 123 mg larotrectinib sulfate.

Oral Solution

- 20 mg/mL: clear yellow to orange solution. 20 mg/mL larotrectinib is equivalent to 24.6 mg/mL larotrectinib sulfate.

4 CONTRAINDICATIONS

None.

5 WARNINGS AND PRECAUTIONS

5.1 Neurotoxicity

Among the 176 patients who received VITRAKVI, neurologic adverse reactions of any grade occurred in 53% of patients, including Grade 3 and Grade 4 neurologic adverse reactions in 6% and 0.6% of patients, respectively [see Adverse Reactions (6.1)]. The majority (65%) of neurologic adverse reactions occurred within the first three months of treatment (range: 1 day to 2.2 years). Grade 3 neurologic adverse reactions included delirium (2%), dysarthria (1%), dizziness (1%), gait disturbance (1%), and paresthesia (1%). Grade 4 encephalopathy (0.6%) occurred in a single patient. Neurologic adverse reactions leading to dose modification included dizziness (3%), gait disturbance (1%), delirium (1%), memory impairment (1%), and tremor (1%).

Advise patients and caretakers of these risks with VITRAKVI. Advise patients not to drive or operate hazardous machinery if they are experiencing neurologic adverse reactions. Withhold or permanently discontinue VITRAKVI based on the severity. If withheld, modify the VITRAKVI dosage when resumed [see Dosage and Administration (2.3)].

5.2 Hepatotoxicity

Among the 176 patients who received VITRAKVI, increased transaminases of any grade occurred in 45%, including Grade 3 increased AST or ALT in 6% of patients [see Adverse Reactions (6.1)]. One patient (0.6%) experienced Grade 4 increased ALT. The median time to onset of increased AST was 2 months (range: 1 month to 2.6 years). The median time to onset of increased ALT was 2 months (range: 1 month to 1.1 years). Increased AST and ALT leading to dose modifications occurred in 4% and 6% of patients, respectively. Increased AST or ALT led to permanent discontinuation in 2% of patients.

Monitor liver tests, including ALT and AST, every 2 weeks during the first month of treatment, then monthly thereafter, and as clinically indicated. Withhold or permanently discontinue VITRAKVI based on the severity. If withheld, modify the VITRAKVI dosage when resumed [see Dosage and Administration (2.3)].

5.3 Embryo-Fetal Toxicity

Based on literature reports in human subjects with congenital mutations leading to changes in TRK signaling, findings from animal studies, and its mechanism of action, VITRAKVI can cause fetal harm when administered to a pregnant woman. Larotrectinib resulted in malformations in rats and rabbits at maternal exposures that were approximately 11- and 0.7-times, respectively, those observed at the clinical dose of 100 mg twice daily. Advise women of the potential risk to a fetus. Advise females of reproductive potential to use an effective method of contraception during treatment and for 1 week after the final dose of VITRAKVI [see Use in Specific Populations (8.1, 8.3)].

6 ADVERSE REACTIONS

The following clinically significant adverse reactions are described elsewhere in the labeling:

- Neurotoxicity [see Warnings and Precautions (5.1)]
- Hepatotoxicity [see Warnings and Precautions (5.2)]

6.1 Clinical Trial Experience

Because clinical trials are conducted under widely varying conditions, adverse reaction rates observed in the clinical trials of a drug cannot be directly compared to rates in the clinical trials of another drug and may not reflect the rates observed in practice.

Data in WARNINGS AND PRECAUTIONS and below reflects exposure to VITRAKVI in 176 patients, including 70 (40%) patients exposed for greater than 6 months and 35 (20%) patients exposed for greater than 1 year. VITRAKVI was studied in one adult dose-finding trial [LOXO-TRK-14001 (n = 70)], one pediatric dose-finding trial [SCOUT (n = 43)], and one single arm trial [NAVIGATE (n = 63)]. All patients had an unresectable or metastatic solid tumor and no satisfactory alternative treatment options or disease progression following treatment.

Across these 176 patients, the median age was 51 years (range: 28 days to 82 years); 25% were 18 years or younger; 52% were male; and 72% were White, 11% were Hispanic/Latino, 8% were Black, and 3% were Asian. The most common tumors in order of decreasing frequency were soft tissue sarcoma (16%), salivary gland (11%), lung (10%), thyroid (9%), colon (8%), infantile fibrosarcoma (8%), primary central nervous system (CNS) (7%), or melanoma (5%). NTRK gene fusions were present in 60% of VITRAKVI-treated patients. Most adults (80%) received VITRAKVI 100 mg orally twice daily and 68% of pediatrics (18 years or younger) received VITRAKVI 100 mg/m^2 twice daily up to a maximum dose of 100 mg twice daily. The dose ranged from 50 mg daily to 200 mg twice daily in adults and 9.6 mg/m^2 twice daily to 120 mg/m^2 twice daily in pediatrics [see Pediatric Use (8.4)].

The most common adverse reactions (≥ 20%) in order of decreasing frequency were fatigue, nausea, dizziness, vomiting, anemia, increased AST, cough, increased ALT, constipation, and diarrhea.

The most common serious adverse reactions (≥ 2%) were pyrexia, diarrhea, sepsis, abdominal pain, dehydration, cellulitis, and vomiting. Grade 3 or 4 adverse reactions occurred in 51% of patients; adverse reactions leading to dose interruption or reduction occurred in 37% of patients and 13% permanently discontinued VITRAKVI for adverse reactions.

The most common adverse reactions (1-2% each) that resulted in discontinuation of VITRAKVI were brain edema, intestinal perforation, pericardial effusion, pleural effusion, small intestinal obstruction, dehydration, fatigue, increased ALT, increased AST, enterocutaneous fistula, increased amylase, increased lipase, muscular weakness, abdominal pain, asthenia, decreased appetite, dyspnea, hyponatremia, jaundice, syncope, vomiting, acute myeloid leukemia, and nausea.

The most common adverse reactions (≥ 3%) resulting in dose modification (interruption or reduction) were increased ALT (6%), increased AST (6%), and dizziness (3%). Most (82%) adverse reactions leading to dose modification occurred during the first three months of exposure.

Adverse reactions of VITRAKVI occurring in ≥ 10% of patients and laboratory abnormalities worsening from baseline in ≥ 5% of patients are summarized in Table 2 and Table 3, respectively.

Table 2 Adverse Reactions Occurring in ≥ 10% of Patients Treated with VITRAKVI

Adverse Reaction | VITRAKVI N = 176
Adverse Reaction | All Grades [National Cancer Institute-Common Terminology Criteria for Adverse Events (NCI-CTCAE) v 4.03.] (%) | Grade 3-4 [One Grade 4 adverse reaction of pyrexia.] (%)
General
Fatigue | 37 | 3
Pyrexia | 18 | 1
Edema peripheral | 15 | 0
Gastrointestinal
Nausea | 29 | 1
Vomiting | 26 | 1
Constipation | 23 | 1
Diarrhea | 22 | 2
Abdominal pain | 13 | 2
Nervous System
Dizziness | 28 | 1
Headache | 14 | 0
Respiratory, Thoracic and Mediastinal
Cough | 26 | 0
Dyspnea | 18 | 2
Nasal congestion | 10 | 0
Investigations
Increased weight | 15 | 4
Musculoskeletal and Connective Tissue
Arthralgia | 14 | 1
Myalgia | 14 | 1
Muscular weakness | 13 | 0
Back pain | 12 | 1
Pain in extremity | 12 | 1
Metabolism and Nutrition
Decreased appetite | 13 | 2
Vascular
Hypertension | 11 | 2
Injury, Poisoning and Procedural Complications
Fall | 10 | 1

Table 3 Laboratory Abnormalities Occurring in ≥ 5% Patients Treated with VITRAKVI

Laboratory Abnormality | VITRAKVI [Denominator for each laboratory parameter is based on the number of patients with a baseline and post-treatment laboratory value available which ranged from 170 to 174 patients.]
Laboratory Abnormality | All Grades [NCI-CTCAE v 4.03.] (%) | Grade 3-4 (%)
Chemistry
Increased ALT | 45 | 3
Increased AST | 45 | 3
Hypoalbuminemia | 35 | 2
Increased alkaline phosphatase | 30 | 3
Hematology
Anemia | 42 | 10
Neutropenia | 23 | 7

7 DRUG INTERACTIONS

7.1 Effects of Other Drugs on VITRAKVI

Strong CYP3A4 Inhibitors

Coadministration of VITRAKVI with a strong CYP3A4 inhibitor may increase larotrectinib plasma concentrations, which may result in a higher incidence of adverse reactions [see Clinical Pharmacology (12.3)]. Avoid coadministration of VITRAKVI with strong CYP3A4 inhibitors, including grapefruit or grapefruit juice. If coadministration of strong CYP3A4 inhibitors cannot be avoided, modify VITRAKVI dose as recommended [see Dosage and Administration (2.4)].

Strong CYP3A4 Inducers

Coadministration of VITRAKVI with a strong CYP3A4 inducer may decrease larotrectinib plasma concentrations, which may decrease the efficacy of VITRAKVI [see Clinical Pharmacology (12.3)]. Avoid coadministration of VITRAKVI with strong CYP3A4 inducers, including St. John’s wort. If coadministration of strong CYP3A4 inducers cannot be avoided, modify VITRAKVI dose as recommended [see Dosage and Administration (2.5)].

7.2 Effects of VITRAKVI on Other Drugs

Sensitive CYP3A4 Substrates

Coadministration of VITRAKVI with sensitive CYP3A4 substrates may increase their plasma concentrations, which may increase the incidence or severity of adverse reactions [see Clinical Pharmacology (12.3)]. Avoid coadministration of VITRAKVI with sensitive CYP3A4 substrates. If coadministration of these sensitive CYP3A4 substrates cannot be avoided, monitor patients for increased adverse reactions of these drugs.

8 USE IN SPECIFIC POPULATIONS

8.1 Pregnancy

Risk Summary

Based on literature reports in human subjects with congenital mutations leading to changes in TRK signaling, findings from animal studies, and its mechanism of action [see Clinical Pharmacology (12.1)], VITRAKVI can cause embryo-fetal harm when administered to a pregnant woman. There are no available data on VITRAKVI use in pregnant women. Administration of larotrectinib to pregnant rats and rabbits during the period of organogenesis resulted in malformations at maternal exposures that were approximately 11- and 0.7-times, respectively, those observed at the clinical dose of 100 mg twice daily (see Data). Advise pregnant women of the potential risk to a fetus.

In the U.S. general population, the estimated background risk of major birth defects and miscarriage in clinically recognized pregnancies is 2% to 4% and 15% to 20%, respectively.

Data

Human Data

Published reports of individuals with congenital mutations in TRK pathway proteins suggest that decreases in TRK-mediated signaling are correlated with obesity, developmental delays, cognitive impairment, insensitivity to pain, and anhidrosis.

Animal Data

Larotrectinib crosses the placenta in animals. Larotrectinib did not result in embryolethality at maternally toxic doses [up to 40 times the human exposure based on area under the curve (AUC) at the clinical dose of 100 mg twice daily] in embryo-fetal development studies in pregnant rats dosed during the period of organogenesis; however, larotrectinib was associated with fetal anasarca in rats from dams treated at twice-daily doses of 40 mg/kg [11 times the human exposure (AUC) at the clinical dose of 100 mg twice daily]. In pregnant rabbits, larotrectinib administration was associated with omphalocele at twice-daily doses of 15 mg/kg (0.7 times the human exposure at the clinical dose of 100 mg twice daily).

8.2 Lactation

Risk Summary

There are no data on the presence of larotrectinib or its metabolites in human milk and no data on its effects on the breastfed child or on milk production. Because of the potential for serious adverse reactions in breastfed children, advise women not to breastfeed during treatment with larotrectinib and for 1 week after the final dose.

8.3 Females and Males of Reproductive Potential

Pregnancy Testing

Verify pregnancy status in females of reproductive potential prior to initiating VITRAKVI [see Use in Specific Populations (8.1)].

Contraception

VITRAKVI can cause embryo-fetal harm when administered to a pregnant woman [see Use in Specific Populations (8.1)].

Females

Advise female patients of reproductive potential to use effective contraception during treatment with VITRAKVI and for at least 1 week after the final dose.

Males

Advise males with female partners of reproductive potential to use effective contraception during treatment with VITRAKVI and for 1 week after the final dose.

Infertility

Females

Based on histopathological findings in the reproductive tracts of female rats in a 1-month repeated-dose study, VITRAKVI may reduce fertility [See Nonclinical Toxicology (13.1)].

8.4 Pediatric Use

The safety and effectiveness of VITRAKVI in pediatric patients was established based upon data from three multicenter, open-label, single-arm clinical trials in adult or pediatric patients 28 days and older [see Adverse Reactions (6.1), Clinical Studies (14)].

The efficacy of VITRAKVI was evaluated in 12 pediatric patients and is described in the Clinical Studies section [see Clinical Studies (14)]. The safety of VITRAKVI was evaluated in 44 pediatric patients who received VITRAKVI. Of these 44 patients, 27% were 1 month to < 2 years (n = 12), 43% were 2 years to < 12 years (n = 19), and 30% were 12 years to < 18 years (n = 13); 43% had metastatic disease and 57% had locally advanced disease; and 91% had received prior treatment for their cancer, including surgery, radiotherapy, or systemic therapy. The most common cancers were infantile fibrosarcoma (32%), soft tissue sarcoma (25%), primary CNS tumors (20%), and thyroid cancer (9%). The median duration of exposure was 5.4 months (range: 9 days to 1.9 years).

Due to the small number of pediatric and adult patients, the single arm design of clinical studies of VITRAKVI, and confounding factors such as differences in susceptibility to infections between pediatric and adult patients, it is not possible to determine whether differences in the incidence of adverse reactions to VITRAKVI are related to patient age or other factors. Adverse reactions and laboratory abnormalities of Grade 3 or 4 severity occurring more frequently (at least a 5% increase in per-patient incidence) in pediatric patients compared to adult patients were increased weight (11% vs. 2%) and neutropenia (20% vs. 2%). One of the 44 pediatric patients discontinued VITRAKVI due to an adverse reaction (Grade 3 increased ALT).

The pharmacokinetics of VITRAKVI in the pediatric population were similar to those seen in adults [see Clinical Pharmacology (12.3)].

Juvenile Animal Toxicity Data

Larotrectinib was administered in a juvenile toxicity study in rats at twice daily doses of 0.2, 2 and 7.5 mg/kg from postnatal day (PND) 7 to 27 and at twice daily doses of 0.6, 6 and 22.5mg/kg between PND 28 and 70. The dosing period was equivalent to human pediatric populations from newborn to adulthood. The doses of 2/6 mg/kg twice daily [approximately 0.7 times the human exposure (AUC) at the clinical dose of 100 mg twice daily] and 7.5/22.5 mg/kg twice daily (approximately 4 times the human exposure at the clinical dose of 100 mg twice daily) resulted in mortality between PND 9 to 99; a definitive cause of death was not identified in the majority of cases.

The main findings were transient central nervous system-related signs including head flick, tremor, and circling in both sexes. An increase in the number of errors in a maze swim test occurred in females at exposures of approximately 4 times the human exposure (AUC) at the clinical dose of 100 mg twice daily. Decreased growth and delays in sexual development occurred in the mid- and high-dose groups. Mating was normal in treated animals, but a reduction in pregnancy rate occurred at the high-dose of 7.5/22.5 mg/kg twice daily (approximately 4 times the human exposure at the clinical dose of 100 mg twice daily).

8.5 Geriatric Use

Of 176 patients in the overall safety population who received VITRAKVI, 22% of patients were ≥ 65 years of age and 5% of patients were ≥ 75 years of age. Clinical studies of VITRAKVI did not include sufficient numbers of subjects aged 65 and over to determine whether they respond differently from younger subjects.

8.6 Hepatic Impairment

No dose adjustment is recommended for patients with mild hepatic impairment (Child-Pugh A). Larotrectinib clearance was reduced in subjects with moderate (Child-Pugh B) to severe (Child-Pugh C) hepatic impairment [see Clinical Pharmacology (12.3)]. Reduce VITRAKVI dose as recommended [see Dosage and Administration (2.6)].

8.7 Renal Impairment

No dose adjustment is recommended for patients with renal impairment of any severity [see Clinical Pharmacology (12.3)].

11 DESCRIPTION

Larotrectinib is a kinase inhibitor. VITRAKVI (larotrectinib) capsules and oral solution are formulated using larotrectinib sulfate. The molecular formula for larotrectinib sulfate is C21H24F2N6O6S and the molecular weight is 526.51 g/mol for the sulfate salt and 428.44 g/mol for the free base. The chemical name is (3S)-N-{5-[(2R)-2-(2,5-difluorophenyl)-1-pyrrolidinyl]pyrazolo[1,5-a]pyrimidin-3-yl}-3-hydroxy-1-pyrrolidinecarboxamide sulfate. Larotrectinib sulfate has the following chemical structure:

Larotrectinib sulfate is an off-white to pinkish yellow solid that is not hygroscopic. The aqueous solubility of larotrectinib at 37°C is pH dependent (very soluble at pH 1.0 and freely soluble at pH 6.8, according to USP descriptive terms of solubility).

VITRAKVI (larotrectinib) capsules and oral solution are for oral use. Each capsule contains 25 mg or 100 mg larotrectinib (30.7 mg and 123 mg larotrectinib sulfate, respectively) in a hard gelatin capsule. The capsule is composed of gelatin, titanium dioxide, and edible ink.

The oral solution contains 20 mg/mL larotrectinib (24.6 mg/mL larotrectinib sulfate) and the following inactive ingredients: purified water, hydroxypropyl betadex, sucrose, glycerin, sorbitol, citric acid, sodium phosphate, sodium citrate dihydrate, propylene glycol and flavoring. Preserved with methylparaben and potassium sorbate.

12 CLINICAL PHARMACOLOGY

12.1 Mechanism of Action

Larotrectinib is an inhibitor of the tropomyosin receptor kinases (TRK), TRKA, TRKB, and TRKC. In a broad panel of purified enzyme assays, larotrectinib inhibited TRKA, TRKB, and TRKC with IC50 values between 5-11 nM. One other kinase TNK2 was inhibited at approximately 100-fold higher concentration. TRKA, B, and C are encoded by the genes NTRK1, NTRK2, and NTRK3. Chromosomal rearrangements involving in-frame fusions of these genes with various partners can result in constitutively-activated chimeric TRK fusion proteins that can act as an oncogenic driver, promoting cell proliferation and survival in tumor cell lines.

In in vitro and in vivo tumor models, larotrectinib demonstrated anti-tumor activity in cells with constitutive activation of TRK proteins resulting from gene fusions, deletion of a protein regulatory domain, or in cells with TRK protein overexpression. Larotrectinib had minimal activity in cell lines with point mutations in the TRKA kinase domain, including the clinically identified acquired resistance mutation, G595R. Point mutations in the TRKC kinase domain with clinically identified acquired resistance to larotrectinib include G623R, G696A, and F617L.

12.2 Pharmacodynamics

Cardiac Electrophysiology

At a dose 9-fold higher than the recommended adult dose, VITRAKVI does not prolong QTc intervals to any clinically relevant extent.

12.3 Pharmacokinetics

The pharmacokinetics of larotrectinib were studied in healthy subjects and adult and pediatric patients with locally advanced or metastatic solid tumors. In healthy subjects who received a single dose of VITRAKVI capsules, systemic exposure (Cmax and AUC) of larotrectinib was dose proportional over the dose range of 100 mg to 400 mg (1 to 4 times the recommended adult dose) and slightly greater than proportional at doses of 600 mg to 900 mg (6 to 9 times the recommended adult dose). In adult patients who received VITRAKVI capsules 100 mg twice daily in Study LOXO-TRK-14001, peak plasma levels (Cmax) of larotrectinib were achieved at approximately 1 hour after dosing and steady-state was reached within 3 days. Mean steady-state larotrectinib [coefficient of variation (CV%)] for Cmax was 788 (81%) ng/mL and AUC0-24hrwas 4351 (97%) ng*h/mL.

Absorption

The mean absolute bioavailability of VITRAKVI capsules was 34% (range: 32% to 37%). In healthy subjects, the AUC of VITRAKVI oral solution was similar to that of the capsules and the Cmax was 36% higher with the oral solution.

Effect of Food

The AUC of larotrectinib was similar and the Cmax was reduced by 35% after oral administration of a single 100 mg capsule of VITRAKVI to healthy subjects taken with a high-fat meal (approximately 900 calories, 58 grams carbohydrate, 56 grams fat and 43 grams protein) compared to the Cmax and AUC in the fasted state.

Distribution

The mean (CV%) volume of distribution (Vss) of larotrectinib is 48 (38%) L following intravenous administration of larotrectinib in healthy subjects.

Larotrectinib is 70% bound to human plasma proteins in vitro and binding is independent of drug concentrations. The blood-to-plasma concentration ratio is 0.9.

Elimination

The mean (CV%) clearance (CL/F) of larotrectinib is 98 (44%) L/h and the half-life is 2.9 hours following oral administration of VITRAKVI in healthy subjects.

Metabolism

Larotrectinib is metabolized predominantly by CYP3A4. Following oral administration of a single [^14C] radiolabeled 100 mg dose of larotrectinib to healthy subjects, unchanged larotrectinib constituted 19% and an O-linked glucuronide constituted 26% of the major circulating radioactive drug components in plasma.

Excretion

Following oral administration of a single [^14C] radiolabeled 100 mg dose of larotrectinib to healthy subjects, 58% (5% unchanged) of the administered radioactivity was recovered in feces and 39% (20% unchanged) was recovered in urine.

Specific Populations

Age (range: 28 days to 82 years), sex, and body weight (range: 3.8 kg to 179 kg) had no clinically meaningful effect on the pharmacokinetics of larotrectinib.

Pediatric Patients

In pediatric patients, the larotrectinib geometric mean (%CV) AUC0-24hr by age subgroup was: 3348 (66%) ng*h/mL in patients 1 month to < 2 years (n = 9), 4135 (36%) ng*h/mL in patients 2 to < 12 years (n = 15), and 3108 (69%) ng*h/mL and in patients 12 to < 18 years (n = 9).

Patients with Renal Impairment

Following oral administration of a single 100 mg dose of VITRAKVI capsules in subjects with end-stage renal disease (e.g., subjects who required dialysis), the AUC0-INF of larotrectinib increased 1.5-fold and Cmax increased 1.3-fold as compared to that in subjects with normal renal function (creatinine clearance ≥ 90 mL/min as estimated by Cockcroft-Gault). The pharmacokinetics of VITRAKVI in patients with moderate to severe renal impairment (creatinine clearance ≤ 60 mL/min) have not been studied.

Patients with Hepatic Impairment

Following oral administration of a single 100 mg dose of VITRAKVI capsules, the AUC0-INF of larotrectinib increased 1.3-fold in subjects with mild hepatic impairment (Child-Pugh A), 2-fold in subjects with moderate hepatic impairment (Child-Pugh B) and 3.2-fold in subjects with severe hepatic impairment (Child-Pugh C) as compared to that in subjects with normal hepatic function. The Cmax was similar in subjects with mild and moderate hepatic impairment and the Cmax of larotrectinib increased 1.5-fold in subjects with severe hepatic impairment as compared to that in subjects with normal hepatic function [see Dosage and Administration (2.6), Use in Specific Populations (8.6)].

Drug Interaction Studies

Clinical Studies

Effect of Strong CYP3A Inhibitors: Coadministration of a single 100 mg dose of VITRAKVI capsules with a strong CYP3A inhibitor (itraconazole) increased the AUC0-INF of larotrectinib by 4.3-fold and the Cmax by 2.8-fold as compared to VITRAKVI administered alone [see Dosage and Administration (2.4), Drug Interactions (7.1)]. The effects of CYP3A moderate and weak inhibitors on the pharmacokinetics of larotrectinib have not been studied.

Effect of Strong CYP3A Inducers: Coadministration of a single 100 mg dose of VITRAKVI capsules with a strong CYP3A inducer (rifampin) decreased the AUC0-INF of larotrectinib by 81% and of Cmax by 71% as compared to VITRAKVI administered alone [see Dosage and Administration (2.5), Drug Interactions (7.1)]. The effects of CYP3A weak and moderate inducers on the pharmacokinetics of larotrectinib have not been studied.

Effect of Strong P-glycoprotein (P-gp) Inhibitors: Coadministration of a single 100 mg dose of VITRAKVI capsules with a P-gp inhibitor (rifampin) increased the AUC0-INF of larotrectinib by 1.7-fold and the Cmax by 1.8-fold as compared to VITRAKVI administered alone.

Effect of Larotrectinib on CYP3A4 Substrates: Coadministration of VITRAKVI capsules 100 mg twice daily with a sensitive CYP3A4 substrate (midazolam) increased both the AUC0-INF and Cmax of midazolam by 1.7-fold as compared to midazolam administered alone. The AUC0-INF and Cmax of 1-hydroxymidazolam, the main metabolite of midazolam, were both increased 1.4-fold as compared to when midazolam was administered alone [see Drug Interactions (7.2)].

In Vitro Studies

Effect of Transporter on Larotrectinib: Larotrectinib is a substrate for P-gp and BCRP. Larotrectinib is not a substrate of OAT1, OAT3, OCT1, OCT2, OATP1B1, or OATP1B3.

Effect of Larotrectinib on Transporters: Larotrectinib is not an inhibitor of BCRP, P-gp, OAT1, OAT3, OCT1, OCT2, OATP1B1, OATP1B3, BSEP, MATE1 and MATE2-K at clinically relevant concentrations.

Effect of Larotrectinib on CYP Substrates: Larotrectinib is not an inhibitor or inducer of CYP1A2, CYP2B6, CYP2C8, CYP2C9, CYP2C19, or CYP2D6 at clinically relevant concentrations.

13 NONCLINICAL TOXICOLOGY

13.1 Carcinogenesis, Mutagenesis, Impairment of Fertility

Carcinogenicity studies have not been conducted with larotrectinib. Larotrectinib was not mutagenic in the in vitro bacterial reverse mutation (Ames) assays, with or without metabolic activation, or in the in vitro mammalian mutagenesis assays, with or without metabolic activation. In vivo, larotrectinib was negative in the mouse micronucleus test.

Fertility studies with larotrectinib have not been conducted. In a 3-month repeat-dose toxicity study in the rat, larotrectinib had no effects on spermatogenesis at 75 mg/kg/day (approximately 7 times the human exposure at the 100 mg twice daily dose). Additionally, larotrectinib had no histological effects on the male reproductive tract in rats or monkeys at doses resulting in exposures up to 10 times the human exposure (AUC0-24hr) at the 100 mg twice daily clinical dose.

In a 1-month repeat-dose study in the rat, decreased uterine weight and uterine atrophy were seen at 200 mg/kg/day [approximately 45 times the human exposure (AUC) at the 100 mg twice daily dose]. Fewer corpora lutea and increased incidence of anestrus were also noted at doses ≥ 60 mg/kg/day (approximately 10 times the human exposure at the 100 mg twice daily dose). Decreased fertility occurred in a juvenile animal study [see Use in Specific Populations (8.4)]. There were no findings in female reproductive organs in repeat-dose studies in monkeys at exposures up to 22 times the human exposure at the 100 mg twice daily dose.

13.2 Animal Toxicology and/or Pharmacology

In general toxicology studies conducted in rats and monkeys and in reproductive toxicology studies conducted in rats and rabbits, administration of larotrectinib led to increased food consumption and increased body weight at doses resulting in exposures 0.6 times the human exposure at the 100 mg twice daily clinical dose. Obesity has also been one phenotypic outcome of some human syndromes resulting from congenital mutations in NTRK2 resulting in altered TRK signaling.

14 CLINICAL STUDIES

The efficacy of VITRAKVI was evaluated in pediatric and adult patients with unresectable or metastatic solid tumors with a NTRK gene fusion enrolled in one of three multicenter, open-label, single-arm clinical trials: Study LOXO-TRK-14001 (NCT02122913), SCOUT (NCT02637687), and NAVIGATE (NCT02576431). All patients were required to have progressed following systemic therapy for their disease, if available, or would have required surgery with significant morbidity for locally advanced disease.

Adult patients received VITRAKVI 100 mg orally twice daily and pediatric patients (18 years or younger) received VITRAKVI 100 mg/m^2 up to a maximum dose of 100 mg orally twice daily until unacceptable toxicity or disease progression. Identification of positive NTRK gene fusion status was prospectively determined in local laboratories using next generation sequencing (NGS) or fluorescence in situ hybridization (FISH). NTRK gene fusions were inferred in three patients with infantile fibrosarcoma who had a documented ETV6 translocation identified by FISH. The major efficacy outcome measures were overall response rate (ORR) and duration of response (DOR), as determined by a blinded independent review committee (BIRC) according to RECIST v1.1.

The assessment of efficacy was based on the first 55 patients with solid tumors with an NTRK gene fusion enrolled across the three clinical trials. Baseline characteristics were: median age 45 years (range 4 months to 76 years); 22% <18 years of age, and 78% ≥18 years of age; 53% male; 67% White; 7% Hispanic/Latino, 4% Asian, 4% Black; and ECOG performance status 0-1 (93%) or 2 (7%). Eighty-two percent of patients had metastatic disease and 18% had locally advanced, unresectable disease. Ninety-eight percent of patients had received prior treatment for their cancer, including surgery, radiotherapy, or systemic therapy. Of these, 82% (n = 45) received prior systemic therapy with a median of two prior systemic regimens and 35% (n = 19) received three or more prior systemic regimens. The most common cancers were salivary gland tumors (22%), soft tissue sarcoma (20%), infantile fibrosarcoma (13%), and thyroid cancer (9%). A total of 50 patients had NTRK gene fusions detected by NGS and 5 patients had NTRK gene fusions detected by FISH.

Efficacy results are summarized in Table 4, 5, and 6.

Table 4 Efficacy Results for Patients with Solid Tumors Harboring NTRK Gene Fusions

Efficacy Parameter | VITRAKVI N = 55
Overall response rate (95% CI) | 75% (61%, 85%)
Complete response rate | 22%
Partial response rate [Includes one pediatric patient with unresectable infantile fibrosarcoma who underwent resection following partial response and who remained disease-free at data cutoff.] | 53%
Duration of response [Median duration of response not reached at time of data cutoff.] | N = 41
Range (months) | 1.6+, 33.2+
% with duration ≥ 6 months | 73%
% with duration ≥ 9 months [3 patients with an ongoing response were followed < 9 months from onset of response.] | 63%
% with duration ≥ 12 months [10 patients with an ongoing response were followed < 12 months from onset of response.] | 39%
+ Denotes ongoing response.

Table 5 Efficacy Results by Tumor Type

Tumor Type | Patients (N=55) | ORR |  | DOR
Tumor Type | Patients (N=55) | % | 95% CI | Range (months)
Soft tissue sarcoma | 11 | 91% | (59%, 100%) | 3.6, 33.2+
Salivary gland | 12 | 83% | (52%, 98%) | 7.7, 27.9+
Infantile fibrosarcoma | 7 | 100% | (59%, 100%) | 1.4+, 10.2+
Thyroid | 5 | 100% | (48%, 100%) | 3.7, 27.0+
Lung | 4 | 75% | (19%, 99%) | 8.2, 20.3+
Melanoma | 4 | 50% | NA | 1.9, 17.5+ [Observed values at data cutoff, not a range.]
Colon | 4 | 25% | NA | 5.6
Gastrointestinal stromal tumor | 3 | 100% | (29%, 100%) | 9.5, 17.3
Cholangiocarcinoma | 2 | SD, NE | NA | NA
Appendix | 1 | SD | NA | NA
Breast | 1 | PD | NA | NA
Pancreas | 1 | SD | NA | NA
NA = not applicable due to small numbers or lack of response; CR = complete response; PR = partial response; NE = not evaluable; SD = stable disease; PD = progressive disease.
+ Denotes ongoing response.

Table 6 Efficacy Results by NTRK Fusion Partner

NTRK Partner [Fusion partners identified in the primary analysis set (N=55) may not represent all potential fusion partners.] | Patients (N=55) | ORR |  | DOR
NTRK Partner [Fusion partners identified in the primary analysis set (N=55) may not represent all potential fusion partners.] | Patients (N=55) | % | 95% CI | Range (months)
ETV6-NTRK3 | 25 | 84% | (64%, 96%) | 3.7, 27.9+
TPM3-NTRK1 | 9 | 56% | (21%, 86%) | 3.7, 10.3+
LMNA-NTRK1 | 5 | 40% | NA | 5.6, 33.2+
Inferred ETV6-NTRK3 | 3 | 100% | (29%, 100%) | 1.4+, 2.7 [Duration of response censored at the time of surgery for one pediatric patient with unresectable infantile fibrosarcoma who underwent resection following partial response and who remained disease-free at data cutoff.]
IRF2BP2-NTRK1 | 2 | CR, PR | NA | 3.7, 20.3+
SQSTM1-NTRK1 | 2 | PR, PR | NA | 9.9, 12.9+
PDE4DIP-NTRK1 | 1 | PR | NA | 3.6+ [Observed values at data cutoff, not a range.]
PPL-NTRK1 | 1 | CR | NA | 12.0+
STRN-NTRK2 | 1 | PR | NA | 5.6
TPM4-NTRK3 | 1 | CR | NA | 23.6
TPR-NTRK1 | 1 | PR | NA | 8.2
TRIM63-NTRK1 | 1 | PR | NA | 1.9+
CTRC-NTRK1 | 1 | SD | NA | NA
GON4L-NTRK1 | 1 | NE | NA | NA
PLEKHA6-NTRK1 | 1 | SD | NA | NA
CR = complete response; PR = partial response; NE = not evaluable; SD = stable disease; NA = not applicable.
+ Denotes ongoing response.

16 HOW SUPPLIED/STORAGE AND HANDLING

Capsules

25 mg: Hard gelatin opaque white capsule size #2 with blue printing of "LOXO" and "LARO 25 mg" on the body of the capsule.

- 60 count bottle NDC# 71777-390-01

100 mg: Hard gelatin opaque white capsule size #0 with blue printing of "LOXO" and "LARO 100 mg" on the body of the capsule.

- 60 count bottle NDC# 71777-391-01

Store capsules at room temperature 20°C to 25°C (68°F to 77°F); temperature excursions between 15°C and 30°C (59°F to 86°F) are permitted [see USP Controlled Room Temperature].

Oral Solution

20 mg/mL: Clear yellow to orange solution.

- 100 mL bottle NDC# 71777-392-01

Refrigerate oral solution at 2°C to 8°C (36°F to 46°F). Do not freeze.

17 PATIENT COUNSELING INFORMATION

Advise the patient to read the FDA-approved patient labeling (Patient Information and Instructions for Use).

Neurotoxicity

Advise patients to notify their healthcare provider if they experience new or worsening neurotoxicity. Advise patients not to drive or operate hazardous machinery if they are experiencing neurologic adverse reactions [see Warnings and Precautions (5.1)].

Hepatotoxicity

Advise patients that they will need to undergo laboratory tests to monitor liver function [see Warnings and Precautions (5.2)].

Embryo-Fetal Toxicity

Advise males and females of reproductive potential of the potential risk to a fetus [see Warnings and Precautions (5.3), Use in Specific Populations (8.1)].

Advise females of reproductive potential to inform their healthcare provider of a known or suspected pregnancy and to use effective contraception during the treatment with VITRAKVI and for at least 1 week after the final dose [see Use in Specific Populations (8.3)].

Advise males with female partners of reproductive potential to use effective contraception during treatment with VITRAKVI and for at least 1 week after the final dose [see Use in Specific Populations (8.3)].

Lactation

Advise women not to breastfeed during treatment with VITRAKVI and for 1 week following the final dose [see Use in Specific Populations (8.2)].

Infertility

Advise females of reproductive potential that VITRAKVI may impair fertility [See Nonclinical Toxicology (13.1)].

Drug Interactions

Advise patients and caregivers to inform their healthcare provider of all concomitant medications, including prescription medicines, over-the-counter drugs, vitamins, and herbal products. Inform patients to avoid St. John’s wort, grapefruit or grapefruit juice while taking VITRAKVI [see Drug Interactions (7.1, 7.2)].

Manufactured for:

Loxo Oncology, Inc.
Stamford, CT 06901

PATIENT INFORMATION
VITRAKVI (vi trak vee)
(larotrectinib)
capsules and oral solution

What is VITRAKVI?
VITRAKVI is a prescription medicine that is used to treat adults and children with solid tumors (cancer) that:

- are caused by certain abnormal NTRK genes and
- have spread or if surgery to remove their cancer is likely to cause severe complications, and
- there is no acceptable treatment option or the cancer grew or spread on other treatment.

Your healthcare provider will perform a test to make sure that VITRAKVI is right for you.
It is not known if VITRAKVI is safe and effective in children younger than 1 month of age.

Before taking VITRAKVI, tell your healthcare provider about all of your medical conditions, including if you:

- have liver problems
- have nervous system (neurological) problems
- are pregnant or plan to become pregnant. VITRAKVI can harm your unborn baby. You should not become pregnant during treatment with VITRAKVI.
  - If you are able to become pregnant, your healthcare provider may do a pregnancy test before you start treatment with VITRAKVI.
  - Females who are able to become pregnant should use effective birth control (contraception) during treatment and for at least 1 week after the final dose of VITRAKVI. Talk to your healthcare provider about birth control methods that may be right for you.
  - Males with female partners who are able to become pregnant should use effective birth control during treatment with VITRAKVI and for at least 1 week after the final dose of VITRAKVI.
- are breastfeeding or plan to breastfeed. It is not known if VITRAKVI passes into your breast milk. Do not breastfeed during treatment and for 1 week after the last dose of VITRAKVI.

Tell your healthcare provider about all the medicines you take, including prescription and over-the-counter medicines, vitamins, and herbal supplements. Certain other medicines may affect how VITRAKVI works. Know the medicines you take. Keep a list of them to show your healthcare provider and pharmacist when you get a new medicine.

How should I take VITRAKVI?

- Take VITRAKVI exactly as your healthcare provider tells you.
- Your healthcare provider may stop treatment or change your dose of VITRAKVI if you have side effects. Do not change your dose or stop taking VITRAKVI unless your healthcare provider tells you.
- VITRAKVI comes in capsules and as an oral solution.
- If your healthcare provider prescribes VITRAKVI oral solution:
  - Your healthcare provider will provide you with the VITRAKVI oral solution and oral syringes or send you to a pharmacy that can provide you with VITRAKVI oral solution and oral syringes.
  - Your healthcare provider should show you how to correctly measure and give a dose of VITRAKVI oral solution.
  - See the detailed Instructions for Use that comes with VITRAKVI oral solution for information about the correct way to measure and give a dose of VITRAKVI oral solution. If you have any questions, talk to your healthcare provider or pharmacist.
- VITRAKVI is usually taken by mouth 2 times a day.
- Swallow VITRAKVI capsules whole. Do not chew or crush the capsules.
- Take VITRAKVI with or without food.
- If you vomit after taking a dose of VITRAKVI, wait and take the next dose at your scheduled time
- If you miss a dose of VITRAKVI, take it as soon as you remember unless your next scheduled dose is due within 6 hours. Take the next dose at your regular time.

If you take too much VITRAKVI, call your healthcare provider.

What should I avoid while taking VITRAKVI?

- VITRAKVI can make you feel dizzy. Do not drive or operate machinery until you know how VITRAKVI affects you.
- Avoid taking St. John’s wort, eating grapefruit, or drinking grapefruit juice during treatment with VITRAKVI.

What are the possible side effects of VITRAKVI?
VITRAKVI may cause serious side effects, including:

- Nervous system problems. Tell your healthcare provider if you develop any symptoms such as confusion, difficulty speaking, dizziness, coordination problems, tingling, numbness, or burning sensation in your hands and feet. Your healthcare provider may temporarily stop treatment, decrease your dose, or permanently stop VITRAKVI if you develop symptoms of a nervous system problem with VITRAKVI.
- Liver problems. Your healthcare provider will do blood tests to check your liver function during treatment with VITRAKVI. Tell your healthcare provider right away if you develop symptoms of liver problems including: loss of appetite, nausea or vomiting, or pain on the upper right side of your stomach area. Your healthcare provider may temporarily stop treatment, decrease your dose, or permanently stop VITRAKVI if you develop liver problems with VITRAKVI.

The most common side effects of VITRAKVI include:

- tiredness
- nausea
- dizziness
- vomiting
- cough
- constipation
- diarrhea

VITRAKVI may affect fertility in females and may affect your ability to become pregnant. Talk to your healthcare provider if this is a concern for you.
These are not all the possible side effects with VITRAKVI. Call your healthcare provider for medical advice about side effects. You may report side effects to FDA at 1-800-FDA-1088.

How should I store VITRAKVI?

- Store VITRAKVI capsules at room temperature between 68°F to 77°F (20°C to 25°C).
- Store VITRAKVI oral solution in the refrigerator between 36° F to 46° F (2° C to 8° C). Do not freeze.
- Throw away (dispose of) any unused VITRAKVI oral solution remaining after 90 days of first opening the bottle.

Keep VITRAKVI and all medicines out of the reach of children.

General information about the safe and effective use of VITRAKVI.
Medicines are sometimes prescribed for purposes other than those listed in a Patient Information leaflet. Do not use VITRAKVI for a condition for which it was not prescribed. Do not give VITRAKVI to other people, even if they have the same symptoms you have. It may harm them. You can ask your healthcare provider or pharmacist for more information about VITRAKVI that is written for health professionals.

What are the ingredients in VITRAKVI?
Active ingredient: larotrectinib
Inactive ingredients:
Capsule: gelatin, titanium dioxide and edible ink
Oral Solution: purified water, hydroxypropyl betadex, sucrose, glycerin, sorbitol, citric acid, sodium phosphate, sodium citrate dihydrate, propylene glycol and flavoring. Preserved with methylparaben and potassium sorbate.

Manufactured for: Loxo Oncology, Inc., Stamford, CT 06901

For more information, go to www.VITRAKVI.com or call 1-888-842-2937

This Patient Information has been approved by the U.S. Food and Drug Administration

Issued: 11/2018

INSTRUCTIONS FOR USE
VITRAKVI (vi trak vee)
(larotrectinib)
oral solution

Read this Instructions for Use before you take or give a dose of VITRAKVI oral solution for the first time and each time you get a refill. There may be new information. This information does not take the place of talking with your healthcare provider about your medical condition or your treatment.
Your healthcare provider should show you how to correctly measure the prescribed dose of VITRAKVI oral solution before you take or give a dose for the first time.
Important information about measuring VITRAKVI oral solution:

- Always use the oral syringes provided with VITRAKVI to make sure that you correctly measure the prescribed dose.
- When you receive VITRAKVI oral solution from your healthcare provider or pharmacist, you will get a box that contains 1 glass bottle of VITRAKVI oral solution and a bottle adaptor. You may receive more than 1 box of VITRAKVI oral solution.
- You will receive five 1 mL or 5 mL oral syringes that are marked to help you correctly measure the prescribed dose of VITRAKVI oral solution. Each oral syringe may be used over a 7-day period. Do not use a household teaspoon to measure the dose.

Supplies needed to take or give a dose of VITRAKVI oral solution

How to prepare a dose of VITRAKVI oral solution:

Step 1: Remove the VITRAKVI oral solution bottle from the box. Place the bottle on a flat work surface. Open the bottle by pushing down firmly on the child-resistant cap and turning it in the direction of the arrow (counter-clockwise) See Figure B. Do not throw away the child-resistant cap.

Step 2: Insert the bottle adaptor by pressing it into the bottle neck and make sure it is secure. See Figure C. Do not remove the bottle adaptor. If the bottle adaptor is missing, talk to your healthcare provider.

Step 3: Remove the oral syringe from the wrapper. Throw the wrapper away in your household trash. The barrel of the oral syringe has markings in milliliters (mL). Look at the markings on the barrel of the oral syringe and find the mL marking that matches the VITRAKVI oral solution dose in mL prescribed by your healthcare provider. See Figure D.

Step 4: With the bottle on your flat work surface, use 1 hand to hold the bottle upright. Using your other hand, push the air out of the oral syringe by pushing the plunger down. Then, insert the tip of the oral syringe into the bottle adaptor at the top of the bottle. See Figure E. The tip of the oral syringe should fit snugly into the hole of the bottle adaptor.

Step 5: Use 1 hand to hold the oral syringe in place. With the other hand, turn the bottle upside down. Pull back on the plunger until the top of the plunger lines up with the marking on the barrel of the oral syringe that matches the dose of VITRAKVI oral solution prescribed by your healthcare provider. See Figure "F". Your dose may be different than the dose shown in Figure F.

Step 6: Check for air bubbles in the oral syringe. If you see air bubbles, push up gently on the plunger to push any large air bubbles back into the bottle. Then, pull back on the plunger to the prescribed dose. See Figure G.

Step 7: Turn the bottle upright again and place it on your work surface. Remove the oral syringe from the bottle adaptor by gently pulling up on the syringe barrel. See Figure H. Do not push on the plunger during this step. The bottle adaptor should stay attached to the bottle.

Giving a dose of VITRAKVI oral solution by mouth:

Step 8: Place the tip of the oral syringe into the child’s mouth against the inside of the cheek. Slowly squirt VITRAKVI oral solution into the mouth by pressing down on the plunger and allow the child to swallow. See Figure I.

- The child should be kept in an upright position for a few minutes right after giving a dose of VITRAKVI.
- If the child spits up a dose or you are not sure the entire dose was given, do not give another dose. Wait until the next scheduled dose.

Step 9: Replace the child-resistant cap on the bottle of VITRAKVI oral solution. Do not remove the bottle adaptor. Close the bottle by turning the bottle cap in the direction of the arrow (clockwise). See Figure J.

Cleaning instructions for oral syringes

Follow the instructions below for cleaning the oral syringe (Step 10 through Step 16). After 7 days of use, throw away the oral syringe in your household trash. Use a new one for the next 7 days.

Step 10: Remove plunger from the barrel of the oral syringe. See Figure K.

Step 11: Rinse the barrel and plunger in warm running water to help ensure that all of the medicine has been removed from the oral syringe. See Figure L.
Do not boil the oral syringe.

Step 12: Re-insert the plunger into the barrel of the oral syringe. See Figure M.

Step 13: Draw warm water several times into the oral syringe and squirt out again until all of the medicine has been removed from the oral syringe. See Figure N.

Step 14: Disassemble the oral syringe, and rinse the barrel and plunger again with warm water. See Figure O.

Step 15: Shake off excess water or wipe off the outside, and the place the barrel and plunger on a clean, dry paper towel to dry. See Figure P.

Step 16: Assemble the oral syringe and store in a clean place until the next use.
Replace the oral syringe after 7 days of use, or if:

- there is any damage to the barrel, plunger, or tip
- the dosage marking is no longer clearly recognizable or
- it becomes difficult to move the plunger

How should I store VITRAKVI oral solution?

- Store VITRAKI oral solution in a refrigerator between 36° F to 46° F (2° C to 8° C). Do not freeze.
- Throw away any unused medicine 90 days after the date of first opening. Write the date that you opened the bottle of VITRAKVI oral solution on the bottle. See Figure Q.

Keep VITRAKVI oral solution and all medicines out of the reach of children.

Talk to your healthcare provider if you have questions about how to use VITRAKVI oral solution.

For more information, go to www.VITRAKVI.com or call 1-888-842-2937.

This Instructions for Use has been approved by the U.S. Food and Drug Administration.

Manufactured for: Loxo Oncology, Inc., Stamford, CT 06901

Issued: November 2018

Package Label - Carton - 25 mg - 60 Capsules

PRINCIPAL DISPLAY PANEL

VITRAKVI®

(larotrectinib) capsules

25 mg

Each capsule contains 25 mg larotrectinib
(equivalent to 30.7 mg larotrectinib sulfate).

-60 capsules
-oral use

Package Label - 25 mg - 60 Capsules

PRINCIPAL DISPLAY PANEL

NDC 71777-390-01

VITRAKVI®

(larotrectinib) capsules

25 mg

Usual Dosage: See prescribing information. Rx only.
60 capsules. Keep out of reach of children.
Store at 20°C to 25°C (68°F to 77°F).
Excursions permitted from 15°C to 30°C (59° to 86°F).

Manufactured for Loxo Omcology, Inc. Stamford, CT 06901 86579626

(01)10371777390012

Bayer

LOXO

Each capsule contains
25 mg larotrectinib
(equivalent to 30.7 mg
larotrectinib sulfate).

Package Label - Carton - 100 mg - 60 Capsules

PRINCIPAL DISPLAY PANEL

VITRAKVI®

(larotrectinib) capsules

100 mg

Each capsule contains 100 mg larotrectinib
(equivalent to 123 mg larotrectinib sulfate).

-60 capsules
-oral use

Package Label - 100 mg - 60 Capsules

PRINCIPAL DISPLAY PANEL

NDC 71777-391-01

VITRAKVI®

(larotrectinib) capsules

100 mg

Usual Dosage: See prescribing information.

Rx only. 60 capsules. Keep out of reach of children.
Store at 20°C to 25°C (68°F to 77°F).
Excursions permitted from 15°C to 30°C (59° to 86°F).

Manufactured for Loxo Omcology, Inc. Stamford, CT 06901 86579634

(01)10371777391019

Bayer

LOXO

Each capsule
contains 100 mg
larotrectinib
(equivalent to
123 mg
larotrectinib
sulfate).

PACKAGE LABEL

Package Label - Carton - 20 mg/mL - 100 mL Oral Solution

PRINCIPAL DISPLAY PANEL

VITRAKVI®

(larotrectinib) oral solution

20 mg/mL

Each bottle contains 100 mL of 20 mg/mL
larotrectinib (equivalent to 24.6 mg/mL
larotrectinib sulfate).

-100 mL oral solution
-oral use

PACKAGE LABEL

Package Label - 20 mg/mL - 100 mL Oral Solution

PRINCIPAL DISPLAY PANEL

NDC 71777-392-01

VITRAKVI®

(larotrectinib) oral solution

20 mg/mL

Usual Dosage: See prescribing information. Keep refrigerated. Store at 2°C to 8°C (36°F to 46°F). Rx only.
Date of first opening ____/____/____. Discard unused portion 90 days after first opening.
100 mL oral solution. Keep out of reach of children.

Manufactured for Loxo Omcology, Inc. Stamford, CT 06901 86659069

(01)10371777392016

Bayer

LOXO

Each bottle contains
100 ml of 20 mg/mL
larotrectinib (equivalent
to 24.6 mg/mL
larotrectinib sulfate).